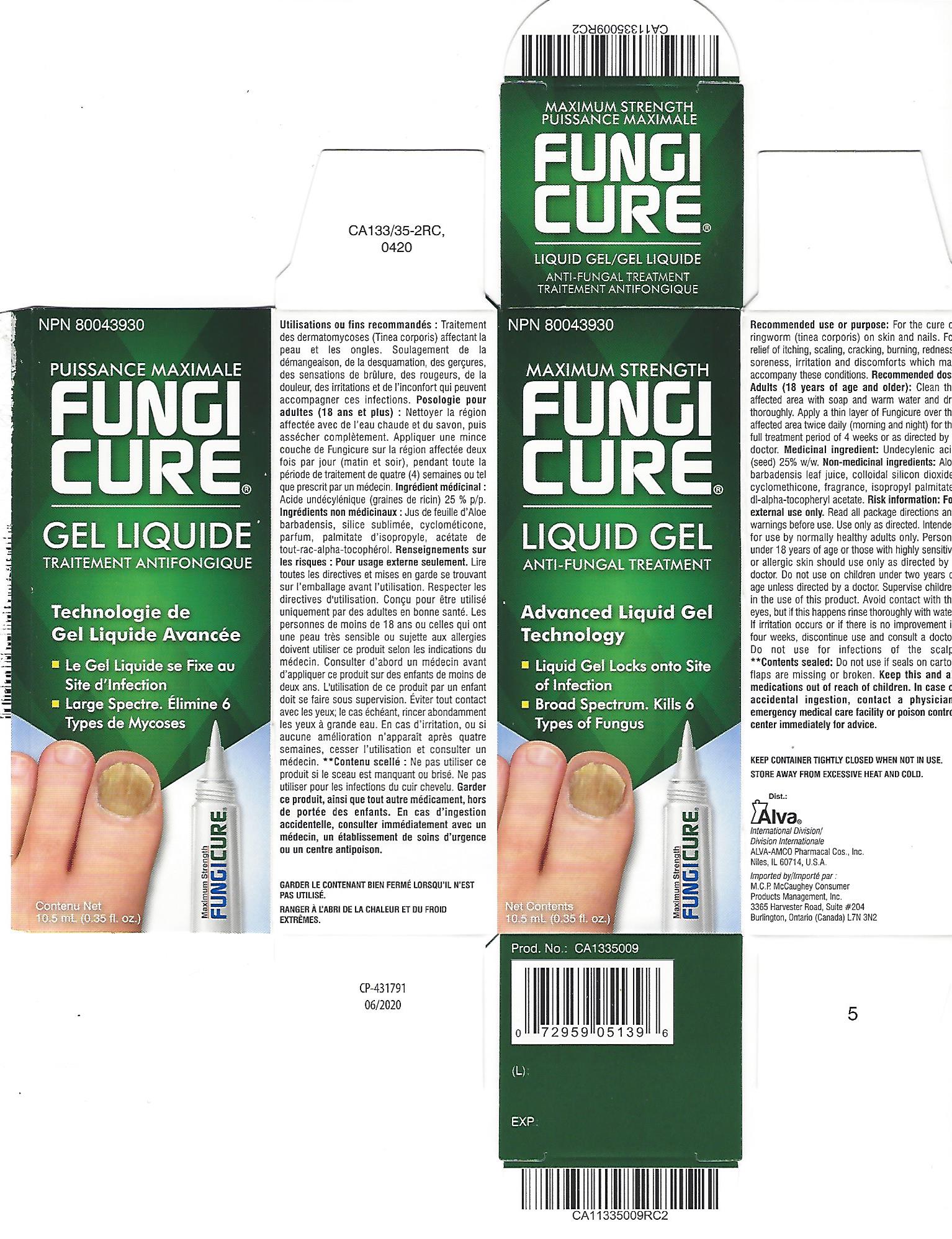 DRUG LABEL: Fungicure LiquidGel
NDC: 52389-633 | Form: GEL
Manufacturer: Kobayashi Healthcare International, Inc.
Category: otc | Type: HUMAN OTC DRUG LABEL
Date: 20250108

ACTIVE INGREDIENTS: UNDECYLENIC ACID 250 mg/1 g
INACTIVE INGREDIENTS: ALOE VERA LEAF; SILICON DIOXIDE; ISOPROPYL PALMITATE; .ALPHA.-TOCOPHEROL ACETATE; CYCLOMETHICONE

Fungicure LiquidGel UDA